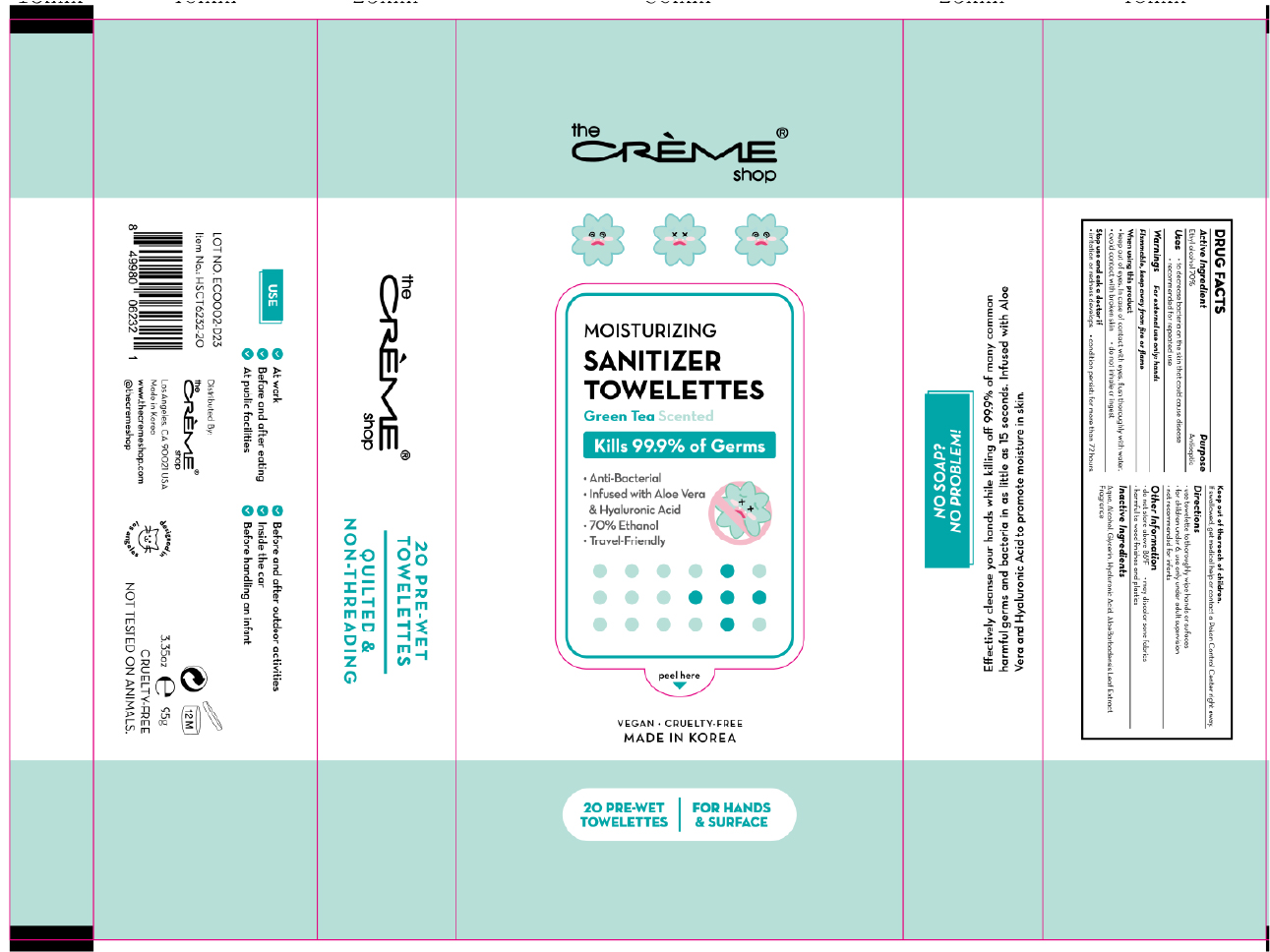 DRUG LABEL: The creme shop Moisturizing Sanitizer Towelettes Green Tea Scented
NDC: 74741-7203 | Form: CLOTH
Manufacturer: MPRBRAIN CO.LTD
Category: otc | Type: HUMAN OTC DRUG LABEL
Date: 20200508

ACTIVE INGREDIENTS: ALCOHOL 0.7 g/1 1
INACTIVE INGREDIENTS: ALOE VERA LEAF; GLYCERIN; HYALURONIC ACID; WATER

The creme shop Moisturizing Sanitizer Towelettes Green Tea Scented : 20 Towelettes
74741-7203-1